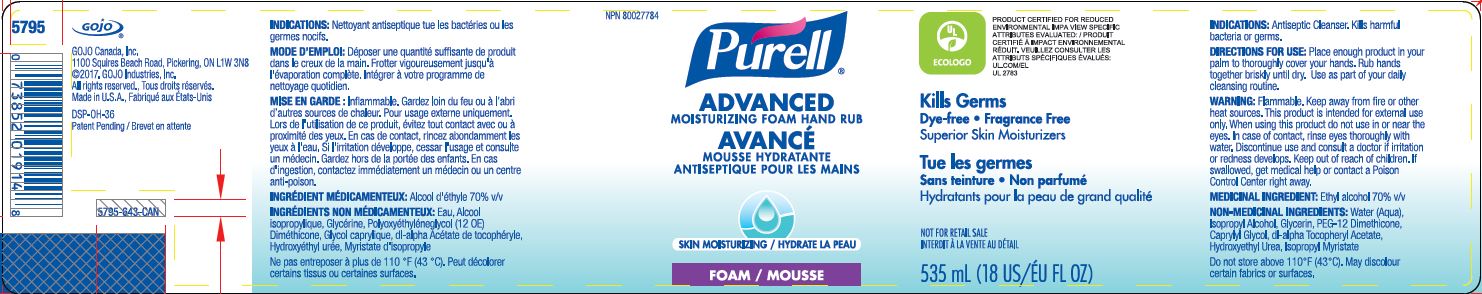 DRUG LABEL: PURELL Advanced Skin Nourishing Instant Hand Sanitizer
NDC: 21749-981 | Form: LIQUID
Manufacturer: GOJO Industries, Inc.
Category: otc | Type: HUMAN OTC DRUG LABEL
Date: 20241231

ACTIVE INGREDIENTS: ALCOHOL 0.7 mL/1 mL
INACTIVE INGREDIENTS: WATER; ISOPROPYL ALCOHOL; GLYCERIN; PEG-12 DIMETHICONE; CAPRYLYL GLYCOL; HYDROXYETHYL UREA; ISOPROPYL MYRISTATE; ALPHA-TOCOPHEROL ACETATE

PURELL Advanced Moisturizing Foam Hand Rub